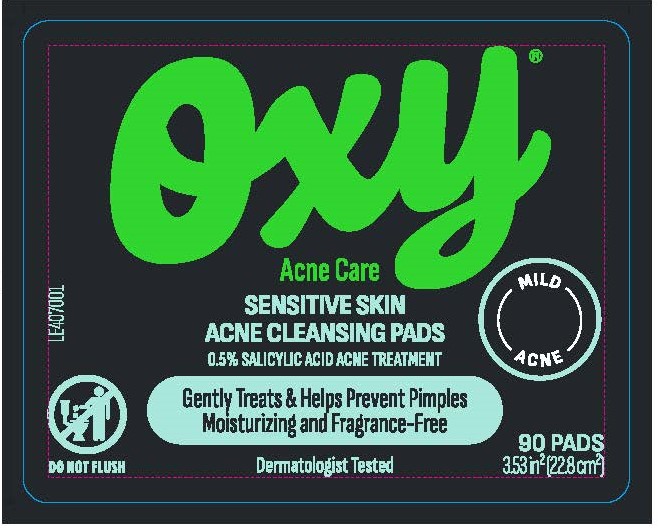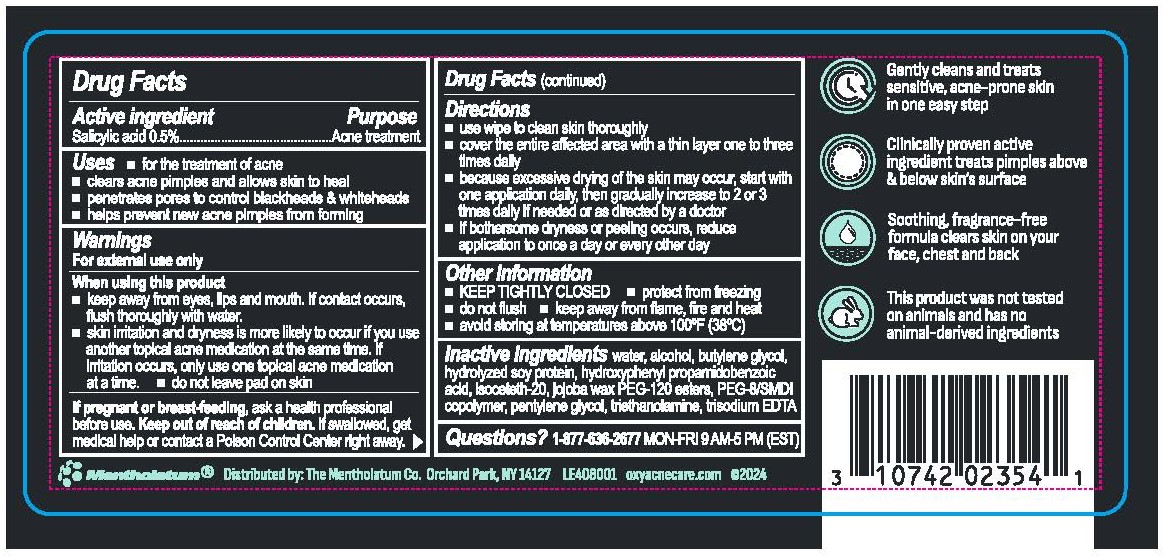 DRUG LABEL: Oxy Sensitive Skin Acne Cleansing Pads
NDC: 10742-1007 | Form: CLOTH
Manufacturer: The Mentholatum Company
Category: otc | Type: HUMAN OTC DRUG LABEL
Date: 20241226

ACTIVE INGREDIENTS: SALICYLIC ACID 5 mg/1 1
INACTIVE INGREDIENTS: HYDROXYPHENYL PROPAMIDOBENZOIC ACID; BUTYLENE GLYCOL; PEG-8/SMDI COPOLYMER; TRIETHANOLAMINE; SIMMONDSIA CHINENSIS (JOJOBA) BUTTER; PENTYLENE GLYCOL; HYDROLYZED SOY PROTEIN (ENZYMATIC; 2000 MW); TRISODIUM EDTA; WATER; ALCOHOL; ISOCETETH-20

Drug Facts - Oxy Sensitive Skin Acne Cleansing Pads

Active ingredients

Salicylic acid 0.5%

Purpose

Acne treatment

Uses

- for the treatment of acne
- clears acne pimples and allows skin to heal
- penetrates pores to control blackheads & whiteheads
- helps prevent new acne pimples from forming

Warnings

For external use only

When using this product

- keep away from eyes, lips and mouth. If contact occurs, flush thoroughly with water.
- skin irritation and dryness is more likely to occur if you use another topical acne medication at the same time. If irritation occurs, only use one topical acne medication at a time.
- do not leave pad on skin

If pregnant or breast feeding,

ask a health professional before use.

Keep out of reach of children

If swallowed, get medical help or contact a Poison Control Center right away.

Directions

- use wipe to clean skin thoroughly
- cover the entire affected area with a thin layer one to three times daily
- because excessive drying of the skin may occur, start with one application daily, then gradually increase to 2 or 3 times daily if needed or as directed by a doctor
- if bothersome dryness or peeling occurs, reduce application to once a day or every other day

Other Information

- KEEP TIGHTLY CLOSED
- protect from freezing
- do not flush
- keep away from flame, fire and heat
- avoid storing at temperatures above 100˚F (38˚C)

Inactive ingredients

water, alcohol, butylene glycol, hydrolyzed soy protein, hydroxyphenyl propamidobenzoic acid, isoceteth-20, jojoba wax PEG-120 esters, PEG-8/SMDI copolymer, pentylene glycol, triethanolamine, trisodium EDTA

Questions?

1-877-636-2677 MON-FRI 9AM-5PM (EST)

Package Label. Principal Display Panel